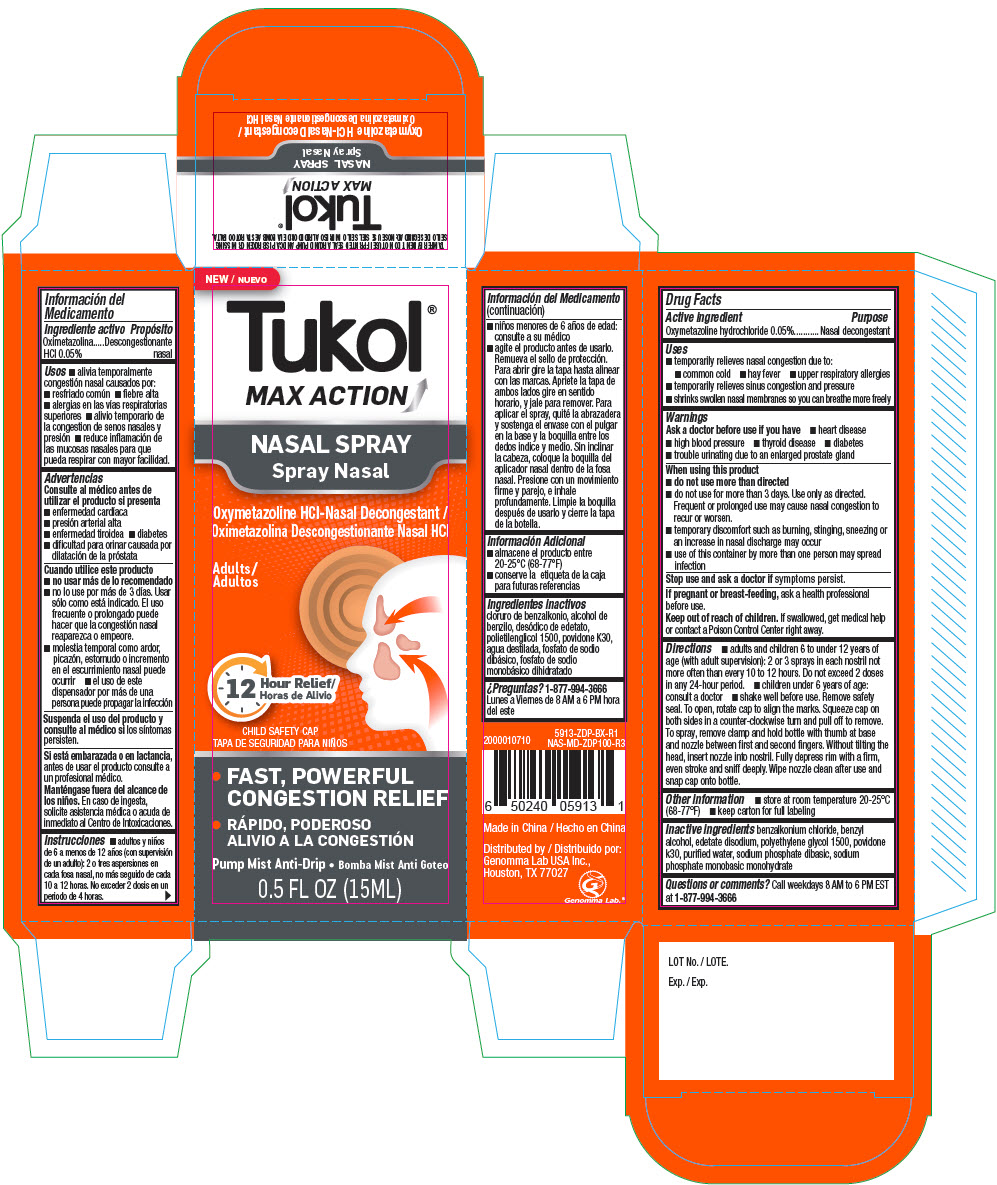 DRUG LABEL: Tukol Max Action
NDC: 50066-518 | Form: LIQUID
Manufacturer: Genomma Lab USA
Category: otc | Type: HUMAN OTC DRUG LABEL
Date: 20250214

ACTIVE INGREDIENTS: oxymetazoline hydrochloride 0.5 mg/1 mL
INACTIVE INGREDIENTS: benzalkonium chloride; benzyl alcohol; SODIUM PHOSPHATE, DIBASIC, ANHYDROUS; SODIUM PHOSPHATE, MONOBASIC, ANHYDROUS; edetate disodium; water

Tukol® Max Action Nasal Spray

Drug Facts

Active ingredient

Oxymetazoline hydrochloride 0.05%

Purpose

Nasal decongestant

Uses

- temporarily relieves nasal congestion due to:
  - common cold
  - hay fever
  - upper respiratory allergies
- temporarily relieves sinus congestion and pressure
- shrinks swollen nasal membranes so you can breathe more freely

Warnings

Ask a doctor before use if you have

- heart disease
- high blood pressure
- thyroid disease
- diabetes
- trouble urinating due to an enlarged prostate gland

When using this product

- do not use more than directed
- do not use for more than 3 days. Use only as directed. Frequent or prolonged use may cause nasal congestion to recur or worsen.
- temporary discomfort such as burning, stinging, sneezing or an increase in nasal discharge may occur
- use of this container by more than one person may spread infection

Stop use and ask a doctor if symptoms persist.

PREGNANCY OR BREAST FEEDING

If pregnant or breast-feeding, ask a health professional before use.

Keep out of reach of children. If swallowed, get medical help or contact a Poison Control Center right away.

Directions

- adults and children 6 to under 12 years of age (with adult supervision): 2 or 3 sprays in each nostril not more often than every 10 to 12 hours. Do not exceed 2 doses in any 24-hour period.
- children under 6 years of age: consult a doctor
- shake well before use. Remove safety seal. To open, rotate cap to align the marks. Squeeze cap on both sides in a counter-clockwise turn and pull off to remove. To spray, remove clamp and hold bottle with thumb at base and nozzle between first and second fingers. Without tilting the head, insert nozzle into nostril. Fully depress rim with a firm, even stroke and sniff deeply. Wipe nozzle clean after use and snap cap onto bottle.

Other information

- store at room temperature 20-25°C (68-77°F)
- keep carton for full labeling

Inactive ingredients

benzalkonium chloride, benzyl alcohol, edetate disodium, polyethylene glycol 1500, povidone k30, purified water, sodium phosphate dibasic, sodium phosphate monobasic monohydrate

Questions or comments?

Call weekdays 8 AM to 6 PM EST at 1-877-994-3666

Distributed by:
Genomma Lab USA Inc.,
Houston, TX 77027

PRINCIPAL DISPLAY PANEL - 15 ML Bottle Carton

NEW

Tukol®
MAX ACTION

NASAL SPRAY

Oxymetazoline HCl-Nasal Decongestant

Adults

12 Hour Relief

CHILD SAFETY CAP

FAST, POWERFUL
CONGESTION RELIEF

Pump Mist Anti-Drip

0.5 FL OZ (15ML)